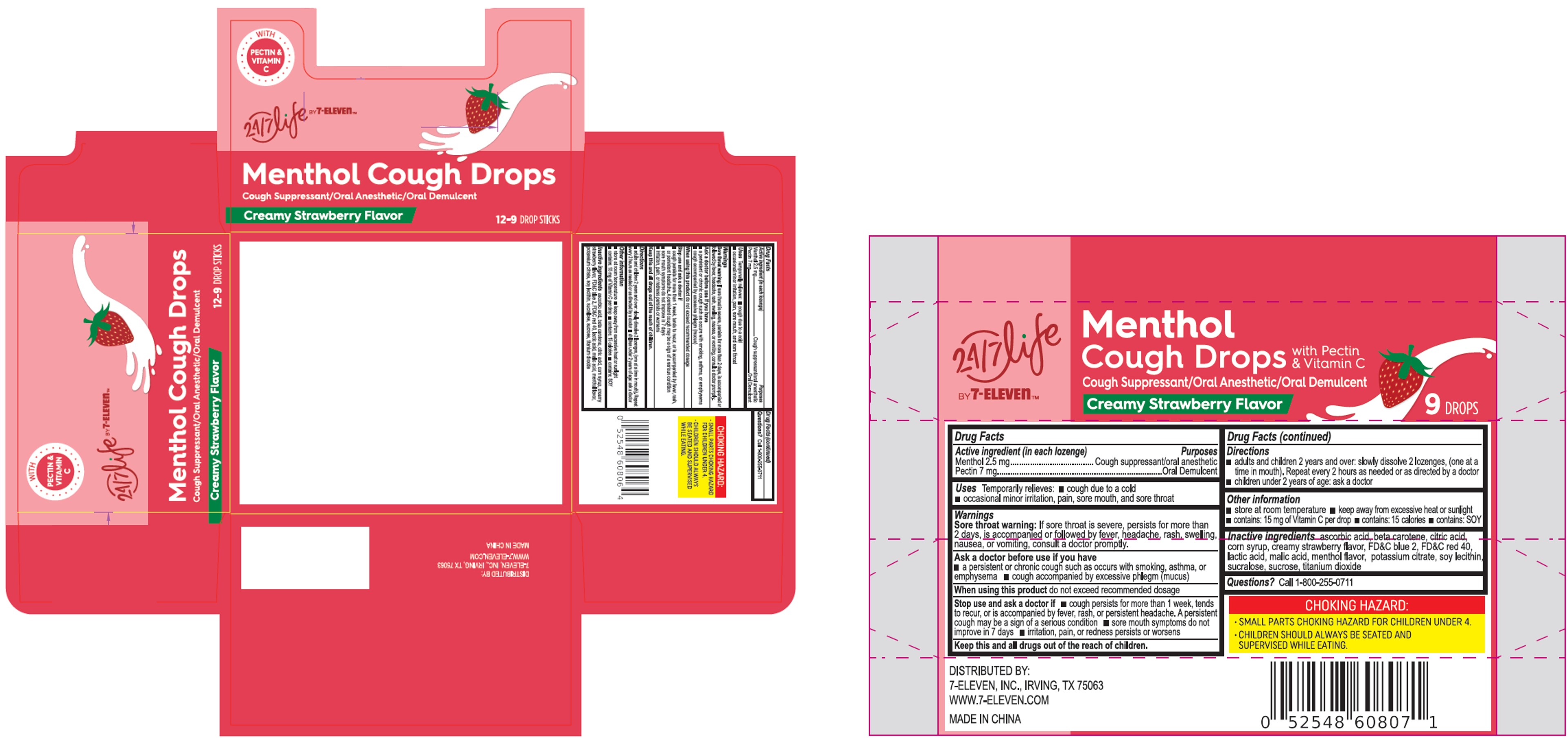 DRUG LABEL: Menthol Cough Drops Creamy Strawberry Flavor
NDC: 10202-012 | Form: LOZENGE
Manufacturer: 7-ELEVEN
Category: otc | Type: HUMAN OTC DRUG LABEL
Date: 20250228

ACTIVE INGREDIENTS: MENTHOL 2.5 mg/1 1; PECTIN 7 mg/1 1
INACTIVE INGREDIENTS: SUCROSE; ASCORBIC ACID; CITRIC ACID MONOHYDRATE; CORN SYRUP; BETA CAROTENE; LACTIC ACID; POTASSIUM CITRATE; LECITHIN, SOYBEAN; FD&C BLUE NO. 2; FD&C RED NO. 40; SUCRALOSE; MALIC ACID; TITANIUM DIOXIDE

7-Eleven MGC Xiamen Creamy Strawberry

Active Ingredient (in each lozenge)

Menthol 2.5 mg

Pactin 7 mg

Purpose

Pectin: oral demulcent

Menthol: cough suppressant, oral anesthetic

Use

temporarily relieves:

- Cough due to a cold
- occasional minor irritation, pain, sore mouth, and sore throat

Warnings

Sore throat warning:If sore throat is severe, persists for more than 2 days, is accompanied or follow by fever, headache, rash, swelling, nausea, or vomiting, consult a doctor promptly.

Ask a doctor before use if you have:■ a persistent or chronic cough such as occurs with smoking, asthma, or emphysema ■ a cough accompanied by excessive phlegm (mucus).

Stop use and ask a doctor if:

- cough persists for more than 1 week, tends to recur, or is accompanied by fever, rash, or persistent headache. A persistent cough may be a sign of a serious condition
- sore mouth symptoms do not improve in 7 days
- irritation, pain, or redness persists or worsens

When using this productdo not exceed recommended dosage

KEEP OUT OF REACH OF CHILDREN

Keep this and all drugs out of the reach of children.

Directions

adults and children 2 ears and over: slowly dissolve 2 drops (one at a time in mouth). Repeat every 2 hours as needed, or as directed by a doctor

children under 2 years: ask a doctor.

Other information

- store at room temperature
- keep awar from excessive heat or sunlight
- contains: 15 mg vitamin C per drop
- contains: 15 calories per drop
- contains: SOY.

Inactive ingredients

ascorbic acid, beta carotene, citric acid, corn syrup, creamy strawberry flavor, FD&C blue 2, FD&C red 40, lactic acid, malic acid, menthol flavor, potassium citrate, soy lecithin, sucralose, sucrose, titanium dioxide

Questions? Call 1-800-255-0711